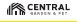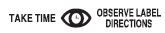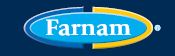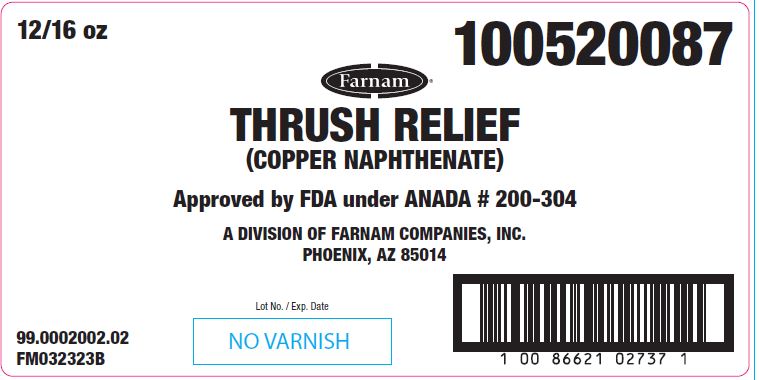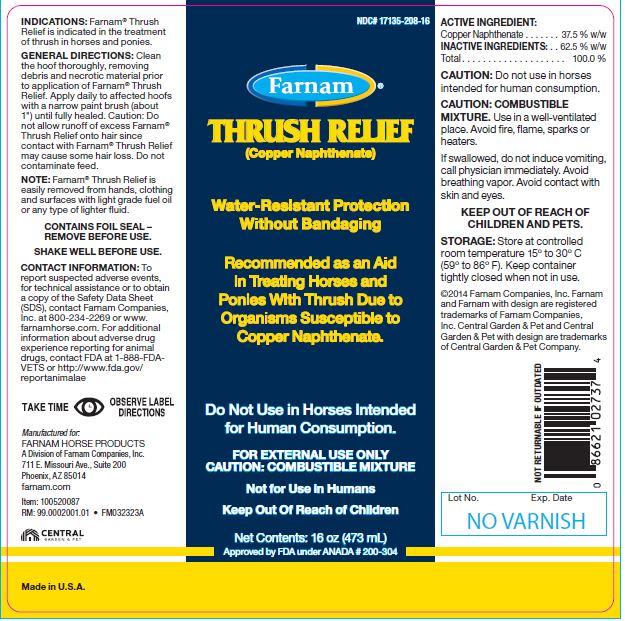 DRUG LABEL: THRUSH RELIEF
NDC: 17135-208 | Form: LIQUID
Manufacturer: Farnam Companies, Inc.
Category: animal | Type: OTC ANIMAL DRUG LABEL
Date: 20231005

ACTIVE INGREDIENTS: COPPER NAPHTHENATE 0.825 g/1 mL

THRUSH RELIEF

INFORMATION FOR OWNERS/CAREGIVERS

(Copper Naphthenate)

Water-Resistant Protection Without Bandaging

Recommended as an Aid in Treating Horses and Ponies with Thrush Due to Organisms Susceptible to Copper Naphthenate.

Do Not Use in Horses Intented for Human Consumption.

FOR EXTERNAL USE ONLY

CAUTION: COMBUSTIBLE MIXTURE

Not for Use in Humans

Keep Out of Reach of Children

Net Contents:

16 oz (473 mL)

Approved by FDA under ANADA # 200-304

INDICATIONS:

Farnam® Thrush Relief is indicated in the treatment of thrush in horses and ponies.

GENERAL DIRECTIONS:

Clean the hoof thoroughly, removing debris and necrotic material prior to application of Farnam® Thrush Relief. Apply daily to affected hoofs with a narrow paint brush (about 1") until fully healed. Caution: Do not allow runoff of excess Farnam® Thrush Relief onto hair since contact with Farnam® Thrush Relief may cause some hair loss. Do not contaminate feed.

INFORMATION FOR OWNERS/CAREGIVERS

NOTE: Farnam® Thrush Relief is easily removed from hands, clothing and surfaces with light grade fuel oil or any type of lighter fluid.

CONTAINS FOIL SEAL – REMOVE BEFORE USE.

SHAKE WELL BEFORE USE.

CONTACT INFORMATION:

To report suspected adverse events, for technical assistance or to obtain a copy of the Safety Data Sheet (SDS), contact Farnam Companies, Inc. at 800-234-2269 or www. farnamhorse.com. For additional information about adverse drug experience reporting for animal drugs, contact FDA at 1-888-FDAVETS or http://www.fda.gov/ reportanimalae

ACTIVE INGREDIENT:

Copper Naphthenate ..........37.5% w/w

INACTIVE INGREDIENTS:

...62.5% W/W

Total .......................100.0%

CAUTION:

Do not use in horses intended for human consumption.

CAUTION: COMBUSTIBLE MIXTURE. Use in a well-ventilated place. Avoid fire, flame, sparks or heaters.

If swallowed, do not induce vomiting, call physician immediately. Avoid breathing vapor. Avoid contact with skin and eyes.

KEEP OUT OF REACH OF CHILDREN AND PETS.

STORAGE:

Store at controlled room temperature 15° to 30°C (59° to 86°F). Keep container tightly closed when not in use.

INFORMATION FOR OWNERS/CAREGIVERS

©2014 Farnam Companies, Inc. Farnam and Farnam with design are registered trademarks of Farnam Companies, Inc. Central Garden & Pet and Central Garden & Pet with design are trademarks of Central Garden & Pet Company.

NOT RETURNABLE IF OUTDATED

Lot No. Exp. Date

Manufactured for:
FARNAM HORSE PRODUCTS
A Division of Farnam Companies, Inc.
711 E. Missouri Ave., Suite 200
Phoenix, AZ 85014
farnam.com
Item: 100520087
RM: 99.0002001.01 • FM032323A

Made in U.S.A.